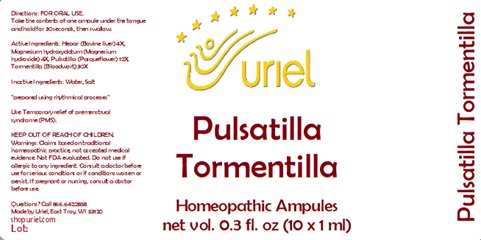 DRUG LABEL: Pulsatilla Tormentilla
NDC: 48951-8098 | Form: LIQUID
Manufacturer: Uriel Pharmacy Inc.
Category: homeopathic | Type: HUMAN OTC DRUG LABEL
Date: 20240426

ACTIVE INGREDIENTS: MAMMAL LIVER 4 [hp_X]/1 mL; MAGNESIUM HYDROXIDE 4 [hp_X]/1 mL; PULSATILLA VULGARIS 12 [hp_X]/1 mL; POTENTILLA ERECTA ROOT 30 [hp_X]/1 mL
INACTIVE INGREDIENTS: WATER; SODIUM CHLORIDE

Pulsatilla Tormentilla

INDICATIONS AND USAGE

Directions: FOR ORAL USE.

DOSAGE AND ADMINISTRATION

Take the contents of one ampule under the tongue and hold for 30 seconds, then swallow.

ACTIVE INGREDIENT

Active Ingredients: Hepar (Bovine liver) 4X, Magnesium hydroxydatum (Magnesium hydroxide) 4X, Pulsatilla (Pasqueflower) 12X, Tormentilla (Bloodwort) 30X

Inactive Ingredients: Water, Salt

"prepared using rhythmical processes"

PURPOSE

Use: Temporary relief of premenstrual syndrome (PMS).

KEEP OUT OF REACH OF CHILDREN.

WARNINGS

Warnings: Claims based on traditional homeopathic practice, not accepted medical evidence. Not FDA evaluated. Do not use if allergic to any ingredient. Consult a doctor before use for serious conditions or if conditions worsen or persist. If pregnant or nursing, consult a doctor before use.

QUESTIONS

Questions? Call 866.642.2858 Made by Uriel, East Troy, WI 53120 shopuriel.com Lot: